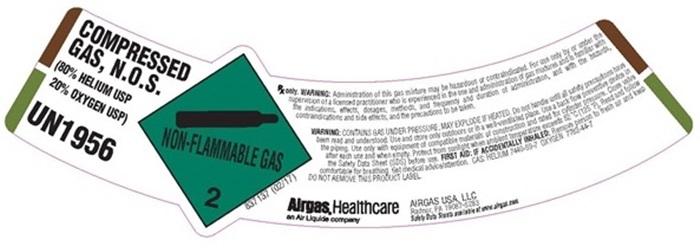 DRUG LABEL: Helium, Oxygen
NDC: 11054-041 | Form: GAS
Manufacturer: AIRGAS USA, LLC
Category: prescription | Type: HUMAN PRESCRIPTION DRUG LABEL
Date: 20241001

ACTIVE INGREDIENTS: HELIUM 800 mL/1 L; OXYGEN 200 mL/1 L

Helium Oxygen Mix 80/20 - 041

PACKAGE LABEL

COMPRESSED GAS, N.O.S.

(80% HELIUM USP, 20% OXYGEN USP)

UN1956

NON-FLAMMABLE GAS 2

837137 (02/17)

RX only. WARNING: Administration of this gas mixture may be hazardous or contraindicated. For use only by or under the supervision of a licensed practitioner who is experienced in the use and administration of gas mixtures, and is familiar with the indications, effects dosages, methods, and frequency and duration of administration and with the hazards, contraindications and side effects and the precautions to be taken.

WARNING: CONTAINS GAS UNDER PRESSURE: MAY EXPLODE IF HEATED. Do not handle until all safety precautions have been read and understood. Use and store only outdoors or in a well-ventilated place. Use a back-flow preventative device in the piping. Use only with equipment of compatible materials of construction and rated for cylinder pressure. Close valve after each use and when empty. Protect from sunlight when ambient temperature exceeds 52oC/125oF. Read and follow the Safety Data Sheet (SDS) before use. FIRST AID: IF ACCIDENTALLY INHALED: Remove person to fresh air and keep comfortable for breathing. Seek medical advice/attention. CAS HELIUM 7440-59-7 OXYGEN 7782-44-7

DO NOT REMOVE THIS PRODUCT LABEL

Airgas, Healthcare

An Air Liquide Company

AIRGAS USA, LLC

Radnor, PA 19087-5283

Safety Data Sheets available at www. airgas.com